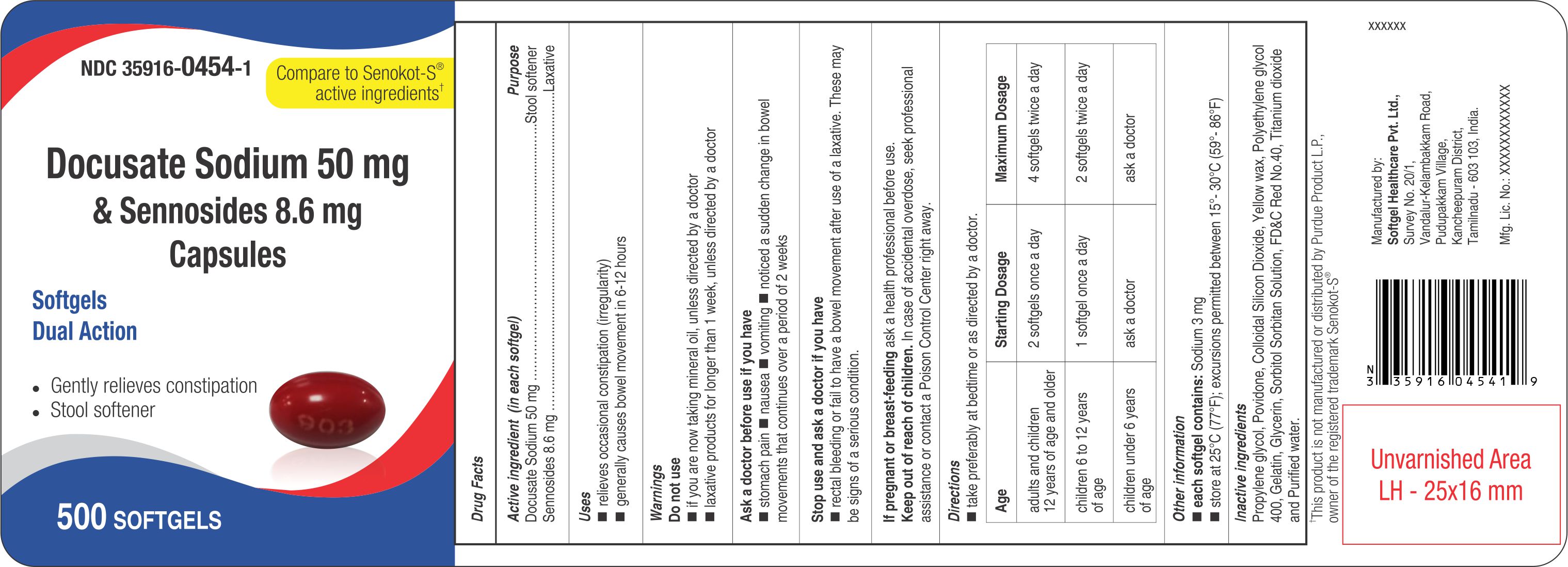 DRUG LABEL: Docusate Sodium and Sennosides
NDC: 35916-0454 | Form: CAPSULE, GELATIN COATED
Manufacturer: SOFTGEL HEALTHCARE PRIVATE LIMITED
Category: otc | Type: HUMAN OTC DRUG LABEL
Date: 20260128

ACTIVE INGREDIENTS: SENNOSIDES 8.6 mg/1 1; DOCUSATE SODIUM 50 mg/1 1
INACTIVE INGREDIENTS: POVIDONE K30; YELLOW WAX; GLYCERIN; PROPYLENE GLYCOL; FD&C RED NO. 40; WATER; GELATIN; SORBITOL; TITANIUM DIOXIDE; SILICON DIOXIDE; POLYETHYLENE GLYCOL 400

Docusate Sodium 50 mg & Sennosides 8.6 mg Capsules (Red)

Active ingredient (in each softgel)

Docusate Sodium 50 mg

Sennosides 8.6 mg

Purpose

Stool softener

Laxative

Uses

- relieves occasional constipation (irregularity)
- generally causes bowel movement in 6-12 hours

Warnings Do not use

- if you are now taking mineral oil, unless directed by a doctor
- laxative products for longer than 1 week, unless directed by a doctor

Ask a doctor before use if you have

- stomach pain
- nausea
- vomiting
- noticed a sudden change in bowel movements that continues over a period of 2 weeks

Stop use and ask a doctor if you have

- rectal bleeding or fail to have a bowel movement after use of a laxative. These may be signs of a serious condition.

If pregnant or breast-feeding

ask a health professional before use.

Keep out of reach of children.

In case of accidental overdose, seek professional assistance or contact a Poison Control Center right away.

Directions

- take preferably at bedtime or as directed by a doctor.

Age | Starting Dosage | Maximum Dosage
adults and children 12 years of age and older | 2 softgels once a day | 4 softgels twice a day
children 6 to 12 years of age | 1 softgel once a day | 2 softgels twice a day
children under 6 years of age | ask a doctor | ask a doctor

Other information

- each softgel contains: Sodium 3 mg
- store at 25°C (77°F); excursions permitted between 15°- 30°C (59°- 86°F)

Inactive ingredients

Propylene glycol, Povidone, Colloidal Silicon Dioxide, Yellow wax, Polyethylene glycol 400, Gelatin, Glycerin, Sorbitol Sorbitan Solution, FD&C Red No.40, Titanium dioxide and Purified water.